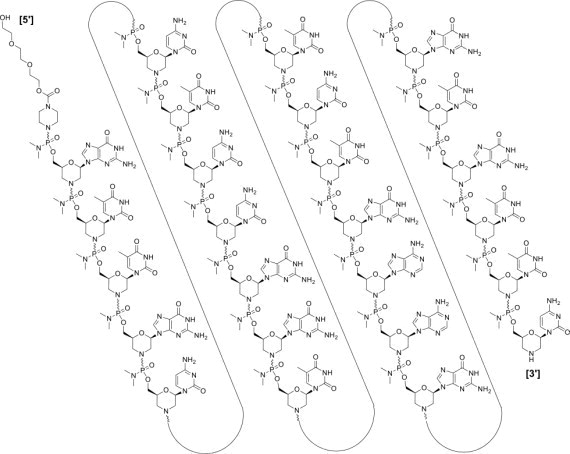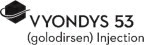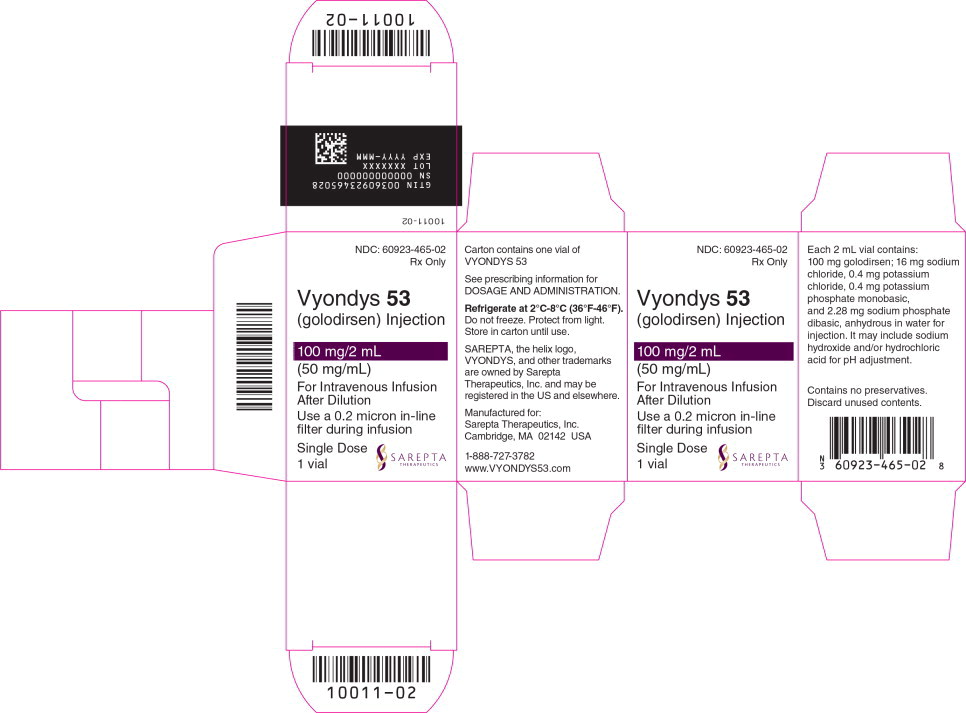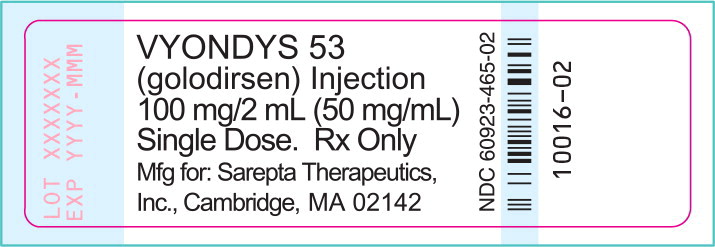 DRUG LABEL: Vyondys 53
NDC: 60923-465 | Form: INJECTION
Manufacturer: Sarepta Therapeutics, Inc.
Category: prescription | Type: HUMAN PRESCRIPTION DRUG LABEL
Date: 20250313

ACTIVE INGREDIENTS: golodirsen 50 mg/1 mL
INACTIVE INGREDIENTS: sodium chloride; potassium chloride; potassium phosphate, monobasic; sodium phosphate, dibasic, anhydrous; sodium hydroxide; hydrochloric acid; water

HIGHLIGHTS OF PRESCRIBING INFORMATION

These highlights do not include all the information needed to use VYONDYS 53 safely and effectively. See full prescribing information for VYONDYS 53.
VYONDYS 53 (golodirsen) injection, for intravenous use
Initial U.S. Approval: 2019

RECENT MAJOR CHANGES

Dosage and Administration (2.4) | 06/2024
Contraindications (4) | 06/2024
Warnings and Precautions (5.1) | 06/2024

1 INDICATIONS AND USAGE

VYONDYS 53 is an antisense oligonucleotide indicated for the treatment of Duchenne muscular dystrophy (DMD) in patients who have a confirmed mutation of the DMD gene that is amenable to exon 53 skipping. This indication is approved under accelerated approval based on an increase in dystrophin production in skeletal muscle observed in patients treated with VYONDYS 53. Continued approval for this indication may be contingent upon verification of a clinical benefit in confirmatory trials. (1)

2 DOSAGE AND ADMINISTRATION

- Serum cystatin C, urine dipstick, and urine protein-to-creatinine ratio should be measured before starting VYONDYS 53 (2.1)
- 30 milligrams per kilogram once weekly (2.2)
- Administer as an intravenous infusion over 35 to 60 minutes via an in-line 0.2 micron filter (2.2, 2.4)
- Dilution required prior to administration (2.3)

3 DOSAGE FORMS AND STRENGTHS

Injection: 100 mg/2 mL (50 mg/mL) in a single-dose vial (3)

4 CONTRAINDICATIONS

VYONDYS 53 is contraindicated in patients with serious hypersensitivity to golodirsen or to any of the inactive ingredients in VYONDYS 53. (4, 5.1)

5 WARNINGS AND PRECAUTIONS

- Hypersensitivity Reactions: Hypersensitivity reactions, including anaphylaxis, rash, pyrexia, pruritus, urticaria, dermatitis, and skin exfoliation have occurred in patients who were treated with VYONDYS 53. If a hypersensitivity reaction occurs, institute appropriate medical treatment and consider slowing the infusion, interrupting or discontinuing the VYONDYS 53 therapy. (2.3, 4, 5.1)
- Kidney Toxicity: Based on animal data, may cause kidney toxicity. Kidney function should be monitored; creatinine may not be a reliable measure of renal function in DMD patients. (5.2, 13.2)

6 ADVERSE REACTIONS

The most common adverse reactions (incidence ≥20% and higher than placebo) were headache, pyrexia, fall, abdominal pain, nasopharyngitis, cough, vomiting, and nausea. (6.1)

To report SUSPECTED ADVERSE REACTIONS, contact Sarepta Therapeutics, Inc. at 1-888-SAREPTA (1-888-727-3782) or FDA at 1-800-FDA-1088 or www.fda.gov/medwatch.

FULL PRESCRIBING INFORMATION

1 INDICATIONS AND USAGE

VYONDYS 53 is indicated for the treatment of Duchenne muscular dystrophy (DMD) in patients who have a confirmed mutation of the DMD gene that is amenable to exon 53 skipping. This indication is approved under accelerated approval based on an increase in dystrophin production in skeletal muscle observed in patients treated with VYONDYS 53 [see Clinical Studies (14)]. Continued approval for this indication may be contingent upon verification of a clinical benefit in confirmatory trials.

2 DOSAGE AND ADMINISTRATION

2.1 Monitoring to Assess Safety

Serum cystatin C, urine dipstick, and urine protein-to-creatinine ratio should be measured before starting VYONDYS 53. Consider measurement of glomerular filtration rate prior to initiation of VYONDYS 53. Monitoring for kidney toxicity during treatment is recommended. Obtain the urine samples prior to infusion of VYONDYS 53 or at least 48 hours after the most recent infusion [see Warnings and Precautions (5.2)].

2.2 Dosing Information

The recommended dosage of VYONDYS 53 is 30 milligrams per kilogram administered once weekly as a 35 to 60-minute intravenous infusion via an in-line 0.2 micron filter.

If a dose of VYONDYS 53 is missed, it may be administered as soon as possible after the scheduled dose.

2.3 Preparation Instructions

VYONDYS 53 is supplied in single-dose vials as a preservative-free concentrated solution that requires dilution prior to administration. Parenteral drug products should be inspected visually for particulate matter and discoloration prior to administration, whenever solution and container permit. Use aseptic technique.

1. Calculate the total dose of VYONDYS 53 to be administered based on the patient's weight and the recommended dose of 30 milligrams per kilogram. Determine the volume of VYONDYS 53 needed and the correct number of vials to supply the full calculated dose.
2. Allow the vials to warm to room temperature. Mix the contents of each vial by gently inverting 2 or 3 times. Do not shake.
3. Visually inspect each vial of VYONDYS 53. The solution is a clear to slightly opalescent, colorless liquid, and may contain trace amounts of small, white to off-white amorphous particles. Do not use if the solution in the vials is cloudy, discolored or contains extraneous particulate matter other than trace amounts of small, white to off-white amorphous particles.
4. With a syringe fitted with a 21-gauge or smaller bore non-coring needle, withdraw the calculated volume of VYONDYS 53 from the appropriate number of vials.
5. Dilute the withdrawn VYONDYS 53 in 0.9% Sodium Chloride Injection, USP, to make a total volume of 100 to150 mL. Gently invert 2 to 3 times to mix. Do not shake. Visually inspect the diluted solution. Do not use if the solution is cloudy, discolored or contains extraneous particulate matter other than trace amounts of small, white to off-white amorphous particles.
6. Administer the diluted solution via an in-line 0.2 micron filter.
7. VYONDYS 53 contains no preservatives and should be administered immediately after dilution. Complete infusion of diluted VYONDYS 53 within 4 hours of dilution. If immediate use is not possible, the diluted product may be stored for up to 24 hours at 2°C to 8°C (36°F to 46°F). Do not freeze. Discard unused VYONDYS 53.

2.4 Administration Instructions

Application of a topical anesthetic cream to the infusion site prior to administration of VYONDYS 53 may be considered.

VYONDYS 53 is administered via intravenous infusion. Flush the intravenous access line with 0.9% Sodium Chloride Injection, USP, prior to and after infusion.

Infuse the diluted VYONDYS 53 over 35 to 60 minutes via an in-line 0.2 micron filter. Do not mix other medications with VYONDYS 53 or infuse other medications concomitantly via the same intravenous access line with VYONDYS 53.

If a hypersensitivity reaction occurs, consider slowing the infusion, interrupting, or discontinuing the VYONDYS 53 therapy [see Contraindications (4), Warnings and Precautions (5.1,) and Adverse Reactions (6.1)].

3 DOSAGE FORMS AND STRENGTHS

VYONDYS 53 is a clear to slightly opalescent, colorless liquid, and may contain trace amounts of small, white to off-white amorphous particles, and available as:

- Injection: 100 mg/2 mL (50 mg/mL) solution in a single-dose vial

4 CONTRAINDICATIONS

VYONDYS 53 is contraindicated in patients with a serious hypersensitivity reaction to golodirsen or to any of the inactive ingredients in VYONDYS 53. Anaphylaxis has occurred in patients receiving VYONDYS 53 [see Warnings and Precautions (5.1)].

5 WARNINGS AND PRECAUTIONS

5.1 Hypersensitivity Reactions

Hypersensitivity reactions, including anaphylaxis, rash, pyrexia, pruritus, urticaria, dermatitis, and skin exfoliation have occurred in VYONDYS 53-treated patients, some requiring treatment. If a hypersensitivity reaction occurs, institute appropriate medical treatment and consider slowing the infusion, interrupting, or discontinuing the VYONDYS 53 therapy and monitor until the condition resolves [see Dosage and Administration (2.4)]. VYONDYS 53 is contraindicated in patients with a history of a serious hypersensitivity reaction to golodirsen or to any of the inactive ingredients in VYONDYS 53 [see Contraindications (4)].

5.2 Kidney Toxicity

Kidney toxicity was observed in animals who received golodirsen [see Use in Specific Populations (8.4)]. Although kidney toxicity was not observed in the clinical studies with VYONDYS 53, the clinical experience with VYONDYS 53 is limited, and kidney toxicity, including potentially fatal glomerulonephritis, has been observed after administration of some antisense oligonucleotides. Kidney function should be monitored in patients taking VYONDYS 53. Because of the effect of reduced skeletal muscle mass on creatinine measurements, creatinine may not be a reliable measure of kidney function in DMD patients. Serum cystatin C, urine dipstick, and urine protein-to-creatinine ratio should be measured before starting VYONDYS 53. Consider also measuring glomerular filtration rate using an exogenous filtration marker before starting VYONDYS 53. During treatment, monitor urine dipstick every month, and serum cystatin C and urine protein-to-creatinine ratio every three months. Only urine expected to be free of excreted VYONDYS 53 should be used for monitoring of urine protein. Urine obtained on the day of VYONDYS 53 infusion prior to the infusion, or urine obtained at least 48 hours after the most recent infusion, may be used. Alternatively, use a laboratory test that does not use the reagent pyrogallol red, as this reagent has the potential to cross react with any VYONDYS 53 that is excreted in the urine and thus lead to a false positive result for urine protein.

If a persistent increase in serum cystatin C or proteinuria is detected, refer to a pediatric nephrologist for further evaluation.

6 ADVERSE REACTIONS

The following serious adverse reactions are described below and elsewhere in the labeling:

- Hypersensitivity Reactions [see Warnings and Precautions (5.1)]

6.1 Clinical Trials Experience

Because clinical trials are conducted under widely varying conditions, adverse reaction rates observed in the clinical trials of a drug cannot be directly compared to rates in the clinical trials of another drug and may not reflect the rates observed in practice.

In the VYONDYS 53 clinical development program, 58 patients received at least one intravenous dose of VYONDYS 53, ranging between 4 mg/kg (0.13 times the recommended dosage) and 30 mg/kg (the recommended dosage). All patients were male and had genetically confirmed Duchenne muscular dystrophy. Age at study entry was 6 to 13 years. Most (86%) patients were Caucasian.

VYONDYS 53 was studied in 2 double-blind, placebo-controlled studies.

In Study 1 Part 1, patients were randomized to receive once-weekly intravenous infusions of VYONDYS 53 (n=8) in four increasing dose levels from 4 mg/kg to 30 mg/kg or placebo (n=4), for at least 2 weeks at each level. All patients who participated in Study 1 Part 1 (n=12) were continued into Study 1 Part 2, an open-label extension, during which they received VYONDYS 53 at a dose of 30 mg/kg IV once weekly [see Clinical Studies (14)].

In Study 2, patients received VYONDYS 53 (n=33) 30 mg/kg or placebo (n=17) IV once weekly for up to 96 weeks, after which all patients received VYONDYS 53 at a dose of 30 mg/kg.

Adverse reactions observed in at least 20% of treated patients in the placebo-controlled sections of Studies 1 and 2 are shown in Table 1.

Table 1: Adverse Reactions That Occurred in At Least 20% of VYONDYS 53-Treated Patients and at a Rate Greater than Placebo in Studies 1 and 2
Adverse Reaction | VYONDYS 53 (N = 41) % | Placebo (N = 21) %
Headache | 41 | 10
Pyrexia | 41 | 14
Fall | 29 | 19
Abdominal pain | 27 | 10
Nasopharyngitis | 27 | 14
Cough | 27 | 19
Vomiting | 27 | 19
Nausea | 20 | 10

Other adverse reactions that occurred at a frequency greater than 5% of VYONDYS 53-treated patients and at a greater frequency than placebo were: administration site pain, back pain, pain, diarrhea, dizziness, ligament sprain, contusion, influenza, oropharyngeal pain, rhinitis, skin abrasion, ear infection, seasonal allergy, tachycardia, catheter site related reaction, constipation, and fracture.

Hypersensitivity reactions have occurred in patients treated with VYONDYS 53 [see Warnings and Precautions (5.1)].

6.2 Postmarketing Experience

The following adverse reactions have been identified during postapproval use of VYONDYS 53. Because these reactions are reported voluntarily from a population of uncertain size, it is not always possible to reliably estimate their frequency or establish a causal relationship to drug exposure.

Immune System Disorders: anaphylaxis [see Contraindications (4) and Warnings and Precautions (5.1)]

8 USE IN SPECIFIC POPULATIONS

8.1 Pregnancy

Risk Summary

There are no human or animal data available to assess the use of VYONDYS 53 during pregnancy. In the U.S. general population, major birth defects occur in 2 to 4% and miscarriage occurs in 15 to 20% of clinically recognized pregnancies.

8.2 Lactation

Risk Summary

There are no human or animal data to assess the effect of VYONDYS 53 on milk production, the presence of golodirsen in milk, or the effects of VYONDYS 53 on the breastfed infant.

The developmental and health benefits of breastfeeding should be considered along with the mother's clinical need for VYONDYS 53 and any potential adverse effects on the breastfed infant from VYONDYS 53 or from the underlying maternal condition.

8.4 Pediatric Use

VYONDYS 53 is indicated for the treatment of Duchenne muscular dystrophy (DMD) in patients who have a confirmed mutation of the DMD gene that is amenable to exon 53 skipping, including pediatric patients [see Clinical Studies (14)].

Intravenous administration of golodirsen (0, 100, 300, or 900 mg/kg) to juvenile male rats once weekly for 10 weeks (postnatal days 14 to 77) did not result in postnatal developmental (e.g., neurobehavioral, immune function, or male reproductive) toxicity. However, at the highest dose tested (900 mg/kg/week), golodirsen resulted in the death of animals because of renal impairment or failure. In surviving animals (including one animal at the lowest dose tested), there was a dose-dependent increase in the incidence and severity of renal tubular effects (including degeneration/regeneration, fibrosis, vacuolation, and dilatation), which correlated with changes in clinical pathology parameters, reflecting a dose-dependent impairment of renal function. In addition, decreases in bone area, mineral content, and mineral density were observed at the highest dose tested (900 mg/kg week) but with no effect on bone growth. A no-effect dose for renal toxicity was not identified; the lowest dose tested (100 mg/kg/week) was associated with plasma exposures (AUC) approximately 2.5 times that in humans at the recommended human dose of 30 mg/kg/week.

8.5 Geriatric Use

DMD is largely a disease of children and young adults; therefore, there is no geriatric experience with VYONDYS 53.

8.6 Patients with Renal Impairment

Renal clearance of golodirsen is reduced in non-DMD adults with renal impairment, based on estimated glomerular filtration rate calculated using the Modification of Diet and Renal Disease (MDRD) equation [see Clinical Pharmacology (12.3)]. However, because of the effect of reduced skeletal muscle mass on creatinine measurements in DMD patients, no specific dosage adjustment can be recommended for DMD patients with renal impairment based on estimated glomerular filtration rate. Patients with known renal function impairment should be closely monitored during treatment with VYONDYS 53.

11 DESCRIPTION

VYONDYS 53 (golodirsen) injection is a sterile, aqueous, preservative-free, concentrated solution for dilution prior to intravenous administration. VYONDYS 53 is a clear to slightly opalescent, colorless liquid, and may contain trace amounts of small, white to off-white amorphous particles. VYONDYS 53 is supplied in single-dose vials containing 100 mg golodirsen (50 mg/mL). VYONDYS 53 is formulated as an isotonic phosphate buffered saline solution with an osmolality of 260 to 320 mOSM and a pH of 7.5. Each milliliter of VYONDYS 53 contains: 50 mg golodirsen; 0.2 mg potassium chloride; 0.2 mg potassium phosphate monobasic; 8 mg sodium chloride; and 1.14 mg sodium phosphate dibasic, anhydrous, in water for injection. The product may contain hydrochloric acid or sodium hydroxide to adjust pH.

Golodirsen is an antisense oligonucleotide of the phosphorodiamidate morpholino oligomer (PMO) subclass. PMOs are synthetic molecules in which the five-membered ribofuranosyl rings found in natural DNA and RNA are replaced by a six-membered morpholino ring. Each morpholino ring is linked through an uncharged phosphorodiamidate moiety rather than the negatively charged phosphate linkage that is present in natural DNA and RNA. Each phosphorodiamidate morpholino subunit contains one of the heterocyclic bases found in DNA (adenine, cytosine, guanine, or thymine). Golodirsen contains 25 linked subunits. The sequence of bases from the 5' end to 3' end is GTTGCCTCCGGTTCTGAAGGTGTTC. The molecular formula of golodirsen is C305H481N138O112P25 and the molecular weight is 8647.28 daltons.

The structure of golodirsen is:

12 CLINICAL PHARMACOLOGY

12.1 Mechanism of Action

Golodirsen is designed to bind to exon 53 of dystrophin pre-mRNA resulting in exclusion of this exon during mRNA processing in patients with genetic mutations that are amenable to exon 53 skipping. Exon 53 skipping is intended to allow for production of an internally truncated dystrophin protein in patients with genetic mutations that are amenable to exon 53 skipping [see Clinical Studies (14)].

12.2 Pharmacodynamics

After treatment with VYONDYS 53, all patients evaluated (n=25) in Study 1 Part 2 [see Clinical Studies (14)] had an increase in skipping of exon 53 demonstrated by reverse transcription polymerase chain reaction (RT-PCR), compared to baseline.

In Study 1 Part 2 [see Clinical Studies (14)], dystrophin levels as assessed by the Sarepta western blot assay increased from 0.10% (SD 0.07) of normal at baseline to 1.02% (SD 1.03) of normal after 48 weeks of treatment with VYONDYS 53. The mean change from baseline in dystrophin after 48 weeks of treatment with VYONDYS 53 was 0.92% (SD 1.01) of normal levels (p<0.001); the median change from baseline was 0.88%. This increase in dystrophin protein expression positively correlated with the level of exon skipping. Dystrophin levels assessed by western blot can be meaningfully influenced by differences in sample processing, analytical technique, reference materials, and quantitation methodologies. Therefore, comparing dystrophin results from different assay protocols will require a standardized reference material and additional bridging studies.

Correct localization of truncated dystrophin to the sarcolemma in muscle fibers of patients treated with golodirsen was demonstrated by immunofluorescence staining.

12.3 Pharmacokinetics

The pharmacokinetics of golodirsen was evaluated in DMD patients following administration of intravenous doses ranging from 4 mg/kg/week to 30 mg/kg/week (i.e., recommended dosage). Golodirsen exposure increased proportionally with dose, with minimal accumulation with once-weekly dosing. Inter-subject variability (as %CV) for Cmax and AUC ranged from 38% to 72%, and 34% to 44%, respectively.

Distribution

Steady-state volume of distribution was similar between DMD patients and healthy subjects. The mean golodirsen steady-state volume of distribution was 668 mL/kg (%CV=32.3) at a dose of 30 mg/kg. Golodirsen plasma protein binding ranged from 33% to 39% and is not concentration dependent.

Elimination

Golodirsen elimination half-life (SD) was 3.4 (0.6) hours, and plasma clearance was 346 mL/hr/kg at the 30 mg/kg dose.

Metabolism

Golodirsen is metabolically stable. No metabolites were detected in plasma or urine.

Excretion

Golodirsen is mostly excreted unchanged in the urine. The elimination half-life (t1/2) was 3.4 hours.

Specific Populations

Age:

The pharmacokinetics of golodirsen have been evaluated in male pediatric DMD patients. There is no experience with the use of VYONDYS 53 in DMD patients 65 years of age or older.

Sex:

Sex effects have not been evaluated; VYONDYS 53 has not been studied in female patients.

Race:

The potential impact of race is not known because 92% of the patients in studies were Caucasians.

Patients with Renal Impairment:

The effect of renal impairment on the pharmacokinetics of golodirsen was evaluated in non-DMD subjects aged 41 to 65 years with Stage 2 chronic kidney disease (CKD) (n=8, estimated glomerular filtration rate (eGFR) ≥60 and <90 mL/min/1.73 m^2) or Stage 3 CKD (n=8, eGFR ≥30 and <60 mL/min/1.73 m^2) and matched healthy subjects (n=8, eGFR ≥90 mL/min/1.73 m^2). Subjects received a single 30 mg/kg IV dose of golodirsen.

In subjects with Stage 2 or Stage 3 CKD, exposure (AUC) increased approximately 1.2-fold and 1.9-fold, respectively. There was no change in the Cmax in subjects with Stage 2 CKD; in subjects with Stage 3 CKD, there was a 1.2-fold increase in Cmax compared with subjects with normal renal function. The effect of Stage 4 or Stage 5 CKD on golodirsen pharmacokinetics and safety has not been studied.

Estimated GFR values derived from MDRD equations and the threshold definitions for various CKD stages in otherwise healthy adults would not be generalizable to pediatric patients with DMD. Therefore, no specific dosage adjustment can be recommended for patients with renal impairment [see Use in Specific Populations (8.6)].

Patients with Hepatic Impairment:

VYONDYS 53 has not been studied in patients with hepatic impairment.

Drug Interaction Studies

Golodirsen did not inhibit CYP1A2, CYP2B6, CYP2C8, CYP2C9, CYP2C19, CYP2D6, or CYP3A4/5 in vitro. Golodirsen was a weak inducer of CYP1A2 and did not induce CYP2B6 or CYP3A4. Golodirsen was not metabolized by human hepatic microsomes and was not a substrate or strong inhibitor of any of the key human drug transporters tested (OAT1, OAT3, OCT2, OATP1B1, MATE1, P-gp, BCRP, and MRP2, OATP1B3 and MATE2-K). Based on in vitro data, golodirsen has a low potential for drug-drug interactions in humans.

13 NONCLINICAL TOXICOLOGY

13.1 Carcinogenesis, Mutagenesis, Impairment of Fertility

Carcinogenesis

Administration of golodirsen to male transgenic (Tg.rasH2) mice (0, 100, 300, or 1000 mg/kg) weekly for 26 weeks by subcutaneous injection and to male rats (0, 30, 100, or 300 mg/kg) weekly for up to 102 weeks by intravenous injection resulted in no increase in neoplasms.

Mutagenesis

Golodirsen was negative in in vitro (bacterial reverse mutation and chromosomal aberration in CHO cells) and in vivo (mouse bone marrow micronucleus) assays.

Impairment of Fertility

Fertility studies in animals were not conducted with golodirsen. No effects of golodirsen on the male reproductive system were observed following weekly subcutaneous administration (0, 120, 300, or 600 mg/kg to male mice or weekly intravenous administration (0, 80, 200, or 400 mg/kg) to male monkeys. Plasma exposure (AUC) at the highest doses tested in mouse and monkey are approximately 10 and 45 times that in humans at the recommended weekly intravenous dose of 30 mg/kg.

13.2 Animal Toxicology and/or Pharmacology

Kidney toxicity was observed in studies in male mice and rats; findings in urinary bladder were observed in male mice.

In male mice, golodirsen was administered weekly for 12 weeks by intravenous injection (0, 12, 120, or 960 mg/kg) or for 26 weeks by subcutaneous injection (0, 120, 300, or 600 mg/kg). In the 12-week study, microscopic findings in kidney (tubular dilatation, basophilic or eosinophilic casts, vacuolation), correlated with increases in serum markers of renal function (e.g., urea nitrogen, creatinine), were observed primarily at the highest dose tested; hypertrophy of the transitional epithelium of the ureter or urinary bladder was observed at all doses. In the 26-week study, renal tubular degeneration and degeneration of the transitional epithelium of the urinary bladder were observed at all doses.

In male rats, intravenous administration of golodirsen (0, 60, 100, 300, or 600 mg/kg) weekly for 13 weeks resulted in tubular degeneration at all but the lowest dose tested; at the high dose, the microscopic changes were accompanied by increases in serum urea nitrogen.

In male monkeys, intravenous administration of golodirsen (0, 80, 200, or 400 mg/kg) weekly for 39 weeks resulted in microscopic changes in kidney (basophilia, dilatation, or mononuclear cell infiltration) at all doses, which correlated with increases in serum markers of renal function (urea nitrogen, creatinine) at the highest dose tested.

14 CLINICAL STUDIES

The effect of VYONDYS 53 on dystrophin production was evaluated in one study in DMD patients with a confirmed mutation of the DMD gene that is amenable to exon 53 skipping (Study 1; NCT02310906).

Study 1 Part 1 was a double-blind, placebo-controlled, dose-titration study in 12 DMD patients. Patients were randomized 2:1 to receive VYONDYS 53 or matching placebo. VYONDYS 53-treated patients received four escalating dose levels, ranging from 4 mg/kg/week (less than the recommended dosage) to 30 mg/kg/week, by intravenous infusion for 2 weeks at each dose level.

Study 1 Part 2 was a 168-week, open-label study assessing the efficacy and safety of VYONDYS 53 at a dose of 30 mg/kg/week in the 12 patients enrolled in Part 1, plus 13 additional treatment-naive patients with DMD amenable to exon 53 skipping. At study entry (either in Part 1 or Part 2), patients had a median age of 8 years and were on a stable dose of corticosteroids for at least 6 months. Efficacy was assessed based on change from baseline in the dystrophin protein level (measured as % of the dystrophin level in healthy subjects, i.e., % of normal) at Week 48 of Part 2. Muscle biopsies were obtained at baseline prior to treatment and at Week 48 of Part 2 in all VYONDYS 53-treated patients (n=25), and were analyzed for dystrophin protein level by Sarepta western blot. Mean dystrophin levels increased from 0.10% (SD 0.07) of normal at baseline to 1.02% (SD 1.03) of normal by Week 48 of Study 1 Part 2, with a mean change in dystrophin of 0.92% (SD 1.01) of normal levels (p<0.001); the median change from baseline was 0.88%.

Individual patient dystrophin levels from Study 1 are shown in Table 2.

Table 2: Dystrophin Expression Sarepta Western Blot by Individual Patient From Study 1
Patient Number | Sarepta Western Blot % Normal Dystrophin |  |  | Patient number | Sarepta Western Blot % Normal Dystrophin
Patient Number | Baseline | Part 2 Week 48 | Change from baseline | Patient number | Baseline | Part 2 Week 48 | Change from baseline
1 | 0.08 | 0.09 | 0.01 | 14 | 0.22 | 0.28 | 0.06
2 | 0.11 | 0.11 | 0.01 | 15 | 0.14 | 0.21 | 0.07
3 | 0.21 | 0.22 | 0.01 | 16 | 0.05 | 0.42 | 0.37
4 | 0.05 | 0.12 | 0.08 | 17 | 0.07 | 1.03 | 0.97
5 | 0.03 | 0.12 | 0.09 | 18 | 0.02 | 1.57 | 1.55
6 | 0.06 | 0.14 | 0.09 | 19 | 0.12 | 1.17 | 1.05
7 | 0.12 | 0.37 | 0.25 | 20 | 0.03 | 1.72 | 1.69
8 | 0.11 | 1.06 | 0.95 | 21 | 0.11 | 1.77 | 1.66
9 | 0.06 | 0.54 | 0.48 | 22 | 0.31 | 4.30 | 3.99
10 | 0.05 | 0.97 | 0.92 | 23 | 0.11 | 0.36 | 0.25
11 | 0.06 | 1.55 | 1.49 | 24 | 0.03 | 0.91 | 0.88
12 | 0.07 | 1.91 | 1.84 | 25 | 0.07 | 1.29 | 1.22
13 | 0.10 | 3.25 | 3.15

16 HOW SUPPLIED/STORAGE AND HANDLING

16.1 How Supplied

VYONDYS 53 injection is supplied in single dose vials. The solution is a clear to slightly opalescent, colorless liquid, and may contain trace amounts of small, white to off-white amorphous particles.

- Single-dose vials containing 100 mg/2mL (50 mg/mL) | NDC 60923-465-02

16.2 Storage and Handling

Store VYONDYS 53 at 2°C to 8°C (36°F to 46°F). Do not freeze. Store in original carton until ready for use to protect from light.

17 PATIENT COUNSELING INFORMATION

Hypersensitivity Reactions

Advise patients and/or caregivers that hypersensitivity reactions, including anaphylaxis, rash, pyrexia, pruritus, urticaria, dermatitis, and skin exfoliation have occurred in patients who were treated with VYONDYS 53. Instruct them to seek immediate medical care should they experience signs and symptoms of hypersensitivity [see Warnings and Precautions (5.1)].

Kidney Toxicity

Inform patients nephrotoxicity has occurred with drugs similar to VYONDYS 53. Advise patients of the importance of monitoring for kidney toxicity by their healthcare providers during treatment with VYONDYS 53 [see Warnings and Precautions (5.2)].

Manufactured for:
Sarepta Therapeutics, Inc.
Cambridge, MA 02142 USA

SAREPTA, SAREPTA THERAPEUTICS, and VYONDYS are trademarks of Sarepta Therapeutics, Inc. registered in the U.S. Patent and Trademark Office and may be registered in various other jurisdictions. VYONDYS 53, and the Vyondys 53 logo are trademarks of Sarepta Therapeutics, Inc.

Principal Display Panel - Carton Label

NDC: 60923-465-02

Rx Only

VYONDYS 53
(golodirsen) Injection

100 mg/2 mL

(50 mg/mL)

For Intravenous Infusion
After Dilution

Use a 0.2 micron in-line
filter during infusion

Single Dose

1 vial

SAREPTA
THERAPEUTICS

Principal Display Panel - Vial Label

NDC: 60923-465-02

VYONDYS 53
(golodirsen) Injection

100 mg/2 mL (50 mg/mL)

Single Dose. Rx Only

Mfg for: Sarepta Therapeutics,
Inc., Cambridge, MA 02142